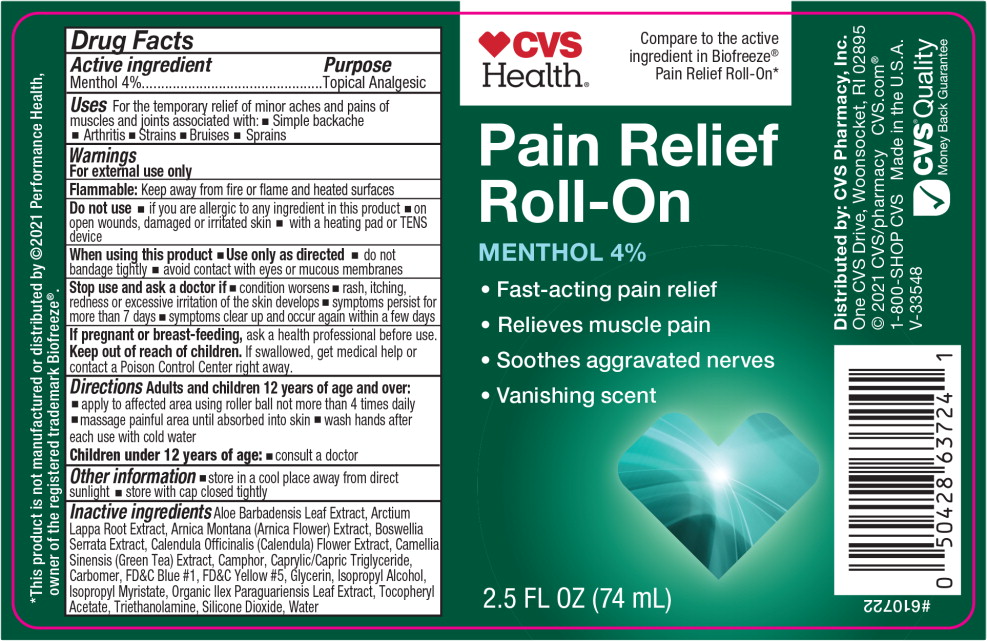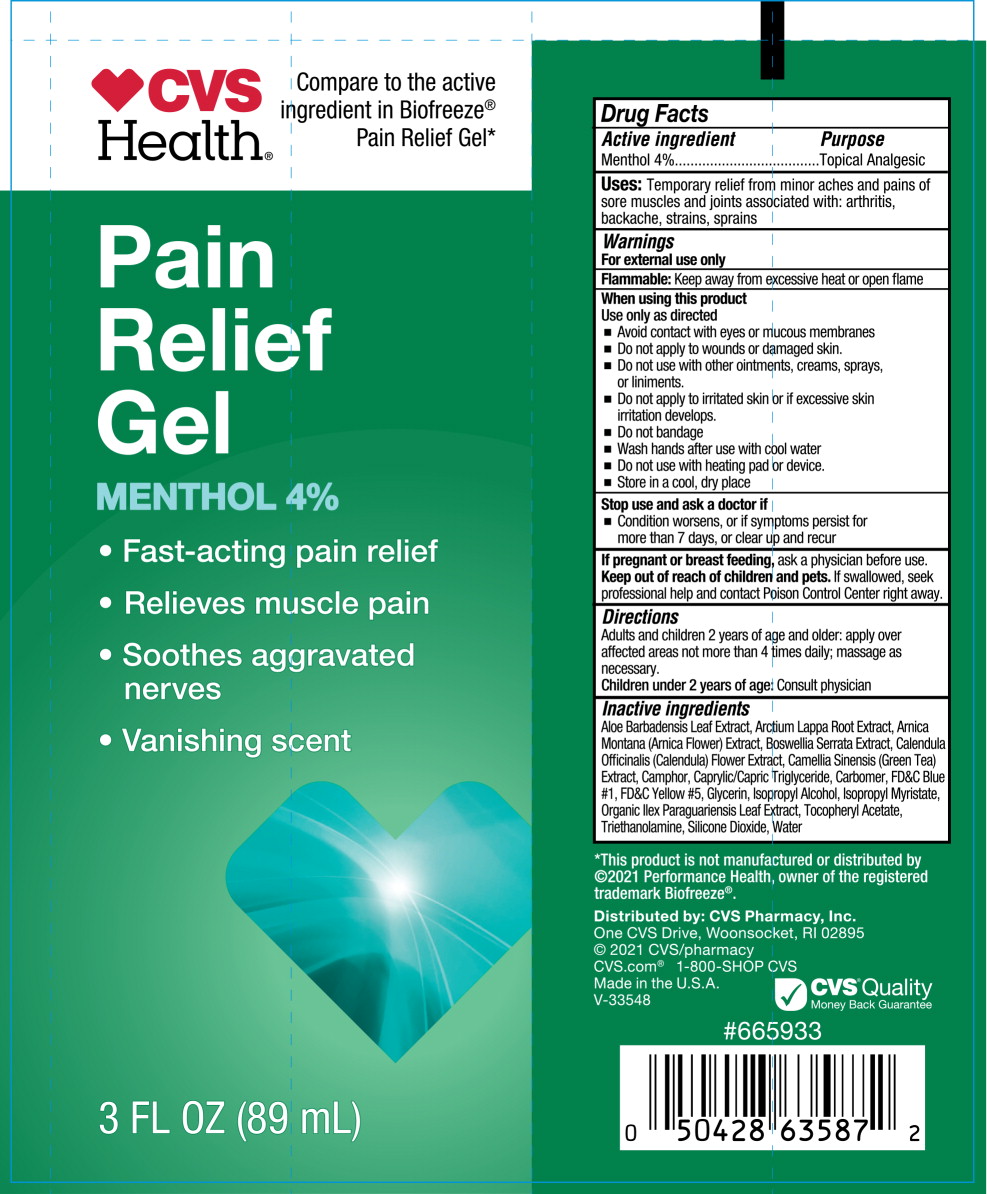 DRUG LABEL: CVS Health Pain Relief
NDC: 66902-920 | Form: GEL
Manufacturer: NATURAL ESSENTIALS, INC.
Category: otc | Type: HUMAN OTC DRUG LABEL
Date: 20241004

ACTIVE INGREDIENTS: MENTHOL, UNSPECIFIED FORM 36 mg/1 mL
INACTIVE INGREDIENTS: ALOE VERA LEAF; ARCTIUM LAPPA ROOT; ARNICA MONTANA FLOWER; INDIAN FRANKINCENSE; CALENDULA OFFICINALIS FLOWER; GREEN TEA LEAF; CAMPHOR (SYNTHETIC); CARBOMER HOMOPOLYMER TYPE C (ALLYL PENTAERYTHRITOL CROSSLINKED); FD&C BLUE NO. 1; FD&C YELLOW NO. 5; GLYCERIN; ISOPROPYL ALCOHOL; ISOPROPYL MYRISTATE; ILEX PARAGUARIENSIS LEAF; SILICON DIOXIDE; .ALPHA.-TOCOPHEROL; TROLAMINE; WATER

Drug Facts

Active ingredient

Menthol 4%

Purpose

Topical Analgesic

Uses

For the temporary relief of minor aches and pains of muscles and joints associated with:

- Simple backache
- Arthritis
- Strains
- Bruises
- Sprains

Warnings

For external use only

Flammable:Keep away from fire or flame and heated surfaces

Do not use

- if you are allergic to any ingredient in this product
- on open wounds, damaged or irritated skin
- with a heating pad or TENS device

When using this product

- Use only as directed
- do not bandage tightly
- avoid contact with eyes or mucous membranes

Stop use and ask a doctor if

- condition worsens
- rash, itching, redness or excessive irritation of the skin develops
- symptoms persist for more than 7 days
- symptoms clear up and occur again within a few days

PREGNANCY OR BREAST FEEDING

If pregnant or breast-feeding,ask a health professional before use.

Keep out of reach of children.If swallowed, get medical help or contact a Poison Control Center right away.

Directions

Adults and children 12 years of age and over:

- apply to affected area using roller ball not more than 4 times daily
- massage painful area until absorbed into skin
- wash hands after each use with cold water

Children under 12 years of age:

- consult a doctor

Other information

- store in a cool place away from direct sunlight
- store with cap closed tightly

Inactive ingredients

Aloe Barbadensis Leaf Extract, Arctium Lappa Root Extract, Arnica Montana (Arnica Flower) Extract, Boswellia Serrata Extract, Calendula Officinalis (Calendula) Flower Extract, Camellia Sinensis (Green Tea) Extract, Camphor, Caprylic/Capric Triglyceride, Carbomer, FD&C Blue #1, FD&C Yellow #5, Glycerin, Isopropyl Alcohol, Isopropyl Myristate, Organic Ilex Paraguariensis Leaf Extract, Tocopheryl Acetate, Triethanolamine, Silicone Dioxide, Water

Principal Display Panel - 74 mL Bottle Label

CVS
Health®

Compare to the active
ingredient in Biofreeze®
Pain Relief Roll-On*

Pain Relief
Roll-On

MENTHOL 4%

- Fast-acting pain relief
- Relieves muscle pain
- Soothes aggravated nerves
- Vanishing scent

2.5 FL OZ (74 mL)

Principal Display Panel - 89 mL Tube Label

CVS
Health®

Compare to the active
ingredient in Biofreeze®
Pain Relief Gel*

Pain
Relief
Gel

MENTHOL 4%

- Fast-acting pain relief
- Relieves muscle pain
- Soothes aggravated nerves
- Vanishing scent

3 FL OZ (89 mL)